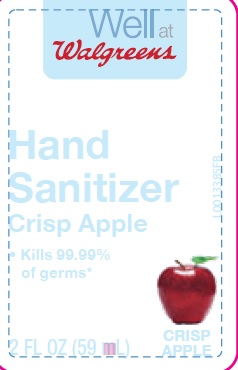 DRUG LABEL: Crisp Apple Hand Sani
NDC: 0363-0663 | Form: LIQUID
Manufacturer: Walgreen CO
Category: otc | Type: HUMAN OTC DRUG LABEL
Date: 20200429

ACTIVE INGREDIENTS: ALCOHOL 585 g/1 mL
INACTIVE INGREDIENTS: SULISOBENZONE; CARBOMER INTERPOLYMER TYPE A (ALLYL SUCROSE CROSSLINKED); POWDERED CELLULOSE; GLYCERIN; HYPROMELLOSES; MANNITOL; FD&C RED NO. 4; FD&C RED NO. 40; VITAMIN A PALMITATE; .ALPHA.-TOCOPHEROL ACETATE; ULTRAMARINE BLUE; WATER

Drug Facts

Active ingredients

Ethyl Alcohol 65%

Purpose

Antiseptic

Use

- to decrease bacteria on the skin that could cause disease
- recommended for repeated use

Warnings

For external use only: hands

Flammable

Keep away from fire or flame.

When using this product

- keep out of eyes. In case of contact with eyes, flush thoroughly with water.
- do not inhale or ingest
- avoid contact with broken skin

Stop use and ask a doctor if

- irritation and redness develops
- condition persists for more than 72 hours

Keep out of reach of children

If swallowed, get medical help or contact a Poison Control Center right away.

Directions

- wet hands thoroughly with product and allow to dry without wiping
- for children under 6, use only under adult supervision
- not recommed for infants

Other Safety Information

- do not store above 105°F
- may discolor some fabrics
- harmful to wood finishes and plastics.

Inactive ingredients

benzophenone-4, carbomer, cellulose, fragrance, glycerin, hydroxypropyl methylcellulose, mannitol, red 4, red 40, retinyl palmitate, tocoperyl acetate, ultamarines, water

claims

Effective at eliminating 99.99% of many common harmful germs and bacteria in as little as 15 seconds

Walgreens Pharmacist Recommended. Walgreens Pharmacist Survey Study, November 2010

Made in U.S.A. with U.S. and foreign components

Adverse reactions

DISTRIBUTED BY: WALGREEN CO.

200 WILMOT RD., DEERFIELD, IL 60015

100%SATISFACTION GUARANTEED

walgreens.com @2014 Walgreen Co.

MADE IN U.S.A. WITH U.S. AND FOREIGN COMPONENTS

663.001/663AB

principal display panel

Well at Walgreens

Hand Sanitizer

Crisp Apple

- Kills 99.99% of germs

2 FL OZ (59 mL)